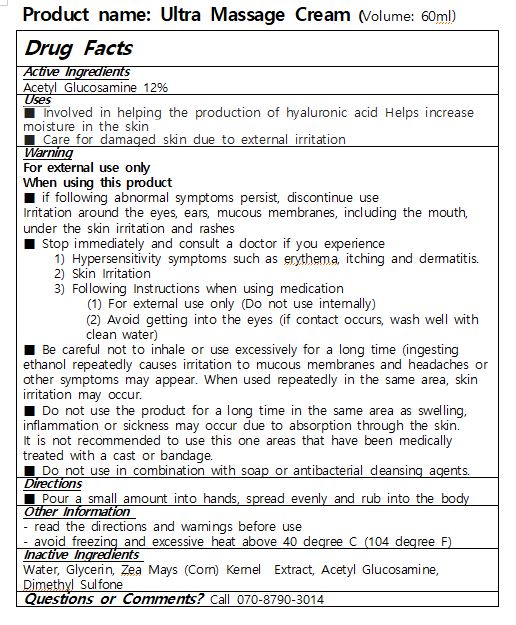 DRUG LABEL: Ultra MassageCream
NDC: 81712-0001 | Form: CREAM
Manufacturer: PK Bio Co., Ltd.
Category: otc | Type: HUMAN OTC DRUG LABEL
Date: 20210330

ACTIVE INGREDIENTS: N-ACETYLGLUCOSAMINE 12 g/100 mL; ADENOSINE 0.04 g/100 mL
INACTIVE INGREDIENTS: GLYCERIN; BUTYLENE GLYCOL

ACTIVE INGREDIENTS

Acetyl Glucosamine

INACTIVE INGREDIENTS

Water, Glycerin, Zea Mays (Corn) Kernel Extract, Acetyl Glucosamine, Dimethyl Sulfone

PURPOSE

■ Involved in helping the production of hyaluronic acid Helps increase moisture in the skin

■ Care for damaged skin due to external irritation

WARNINGS

For external use only

When using this product

■ if following abnormal symptoms persist, discontinue use

Irritation around the eyes, ears, mucous membranes, including the mouth, under the skin irritation and rashes

■ Stop immediately and consult a doctor if you experience

1) Hypersensitivity symptoms such as erythema, itching and dermatitis. 2) Skin Irritation

3) Following Instructions when using medication

(1) For external use only (Do not use internally)

(2) Avoid getting into the eyes (if contact occurs, wash well with clean water)

■ Be careful not to inhale or use excessively for a long time (ingesting ethanol repeatedly causes irritation to mucous membranes and headaches or other symptoms may appear. When used repeatedly in the same area, skin irritation may occur.

■ Do not use the product for a long time in the same area as swelling, inflammation or sickness may occur due to absorption through the skin.

It is not recommended to use this one areas that have been medically treated with a cast or bandage.

■ Do not use in combination with soap or antibacterial cleansing agents.

KEEP OUT OF REACH OF CHILDREN

Uses

Pour a small amount into hands, spread evenly and rub into the body

Directions

for external use only